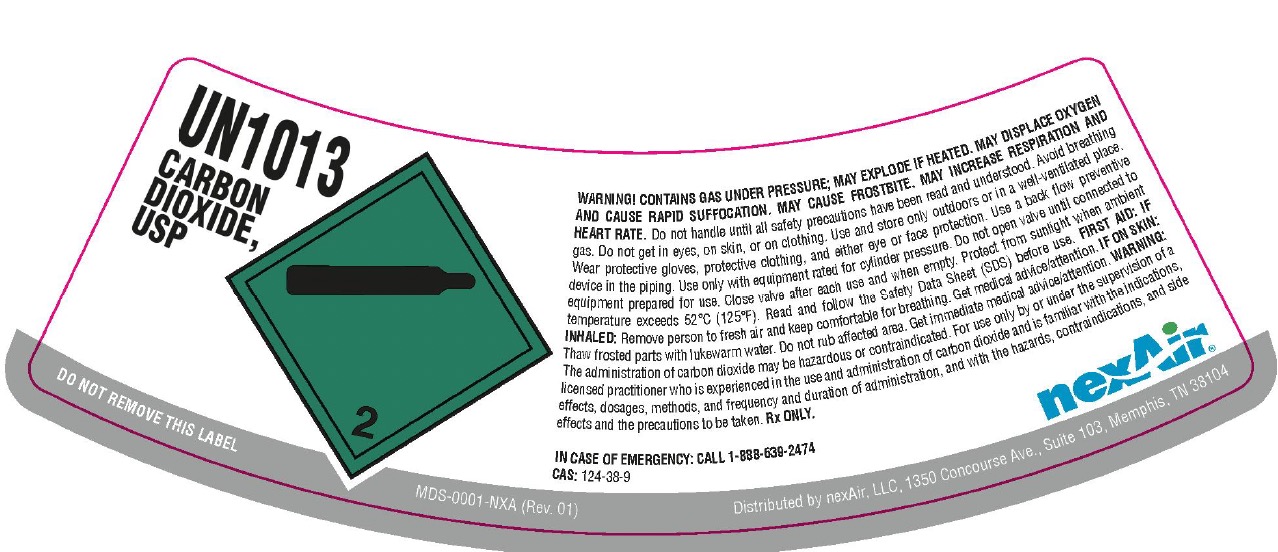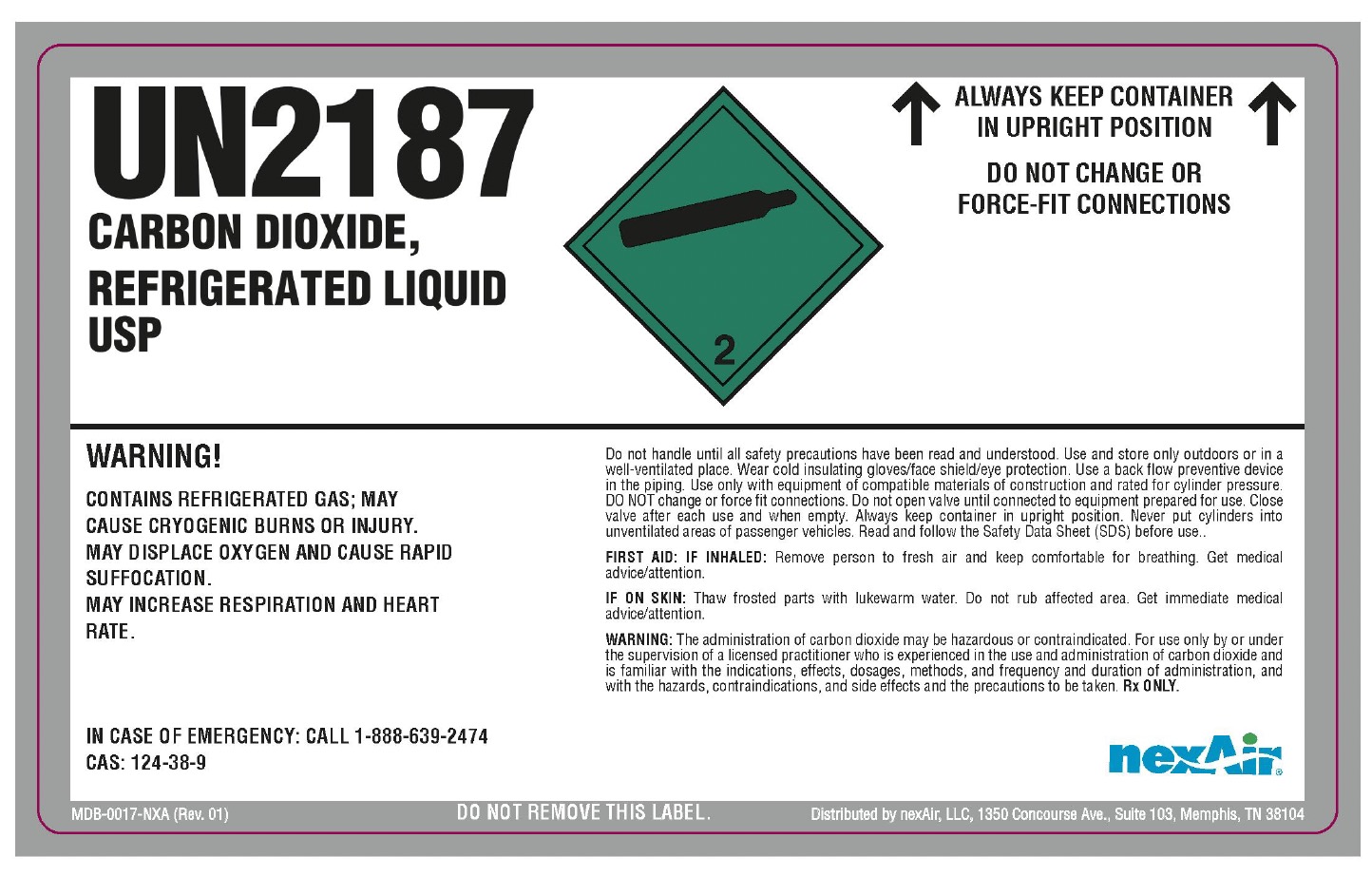 DRUG LABEL: Carbon Dioxide
NDC: 12213-900 | Form: GAS
Manufacturer: NexAir, LLC
Category: prescription | Type: HUMAN PRESCRIPTION DRUG LABEL
Date: 20251031

ACTIVE INGREDIENTS: CARBON DIOXIDE 991 mL/1 L

Carbon Dioxide

PACKAGE LABEL

UN1013

CARBON DIOXIDE, USP

DO NOT REMOVE THIS LABEL

WARNING! CONTAINS GAS UNDER PRESSURE; MAY EXPLODE IF HEATED. MAY DISPLACE OXYGEN AND CAUSE RAPID SUFFOCATION. MAY CAUSE FROSTBITE. MAY INCREASE RESIPRATION AND HEART RATE. Do not handle until all safety precautions have been read and understood. Avoid breathing gas. Do not get in eyes, on skin, or on clothing. Use and store only outdoors or in a well-ventilated place. Wear protective gloves, protective clothing, and either eye or face protection. Use a back flow preventive device in the piping. Use only with equipment rated for cylinder pressure. Do not open valve until connected to equipment prepared for use. Close valve after each use and when empty. Protect from sunlight when ambient temperature exceeds 52 C (125 F). Read and follow the Safety Data Sheet (SDS) before use. FIRST AID: IF INHALED: Remove person to fresh air and keep comfortable for breathing. Get medical advice/attention. IF ON SKIN: Thaw frosted parts with lukewarm water. Do not rub affected area. Get immediate medical advice/attention. WARNING: The administration of carbon dioxide may be hazardous or contraindicated. For use only by or under the supervision of a licensed practitioner who is experienced in the use and administration of carbon dioxide and is familiar with the indications, effects, dosages, methods, and frequency and duration of administration, and with the hazards, contraindications, and side effects and the precautions to be taken. Rx ONLY.

IN CASE OF EMERGENCY: CALL 1-888-639-2474

CAS: 124-38-9

nexAir

Distributed by nexAir, LLC, 1350 Concourse Ave., Suite 103, Memphis, TN 38104

PACKAGE LABEL

UN2187

CARBON DIOXIDE, REFRIGERATED LIQUID USP

WARNING!

CONTAINS REFRIGERATED GAS; MAY CAUSE CRYOGENIC BURNS OR INJURY. MAY DISPLACE OXYGEN AND CAUSE RAPID SUFFOCATION. MAY INCREASE RESPIRATION AND HEART RATE.

IN CASE OF EMERGENCY: CALL 1-888-639-2474

CAS: 124-38-9

ALWAYS KEEP CONTAINER IN UPRIGHT POSITION

DO NOT CHANGE OR FORCE-FIT CONNECTIONS

Do not handle until all safety precautions have been read and understood. Use and store only outdoors or in a well-ventilated place. Wear cold insulating gloves/face shield/eye protection. Use a back flow preventive device in the piping. Use only with equipment of compatible materials of construction and rated for cylinder pressure. DO NOT change or force fit connections. Do not open valve until connected to equipment prepared for use. Close valve after each use and when empty. Always keep container in upright position. Never put cylinders into unventilated areas of passenger vehicles. Read and follow the Safety Data Sheet (SDS) before use.

FIRST AID: IF INHALED: Remove person to fresh air and keep comfortable for breathing. Get medical advice/attention.

IF ON SKIN: Thaw frosted parts with lukewarm water. Do not rub affected area. Get immediate medical advice/attention.

WARNING: The administration of carbon dioxide may be hazardous or contraindicated. For use only by or under the supervision of a licensed practitioner who is experienced in the use and administration of carbon dioxide and is familiar with the indications, effects, dosages, methods, and frequency and duration of administration, and with the hazards, contraindications, and side effects and the precautions to be taken. Rx ONLY.

DO NOT REMOVE THIS LABEL.

nexAir

Distributed by nexAir, LLC, 1350 Concourse Ave., Suite 103, Memphis, TN 38104